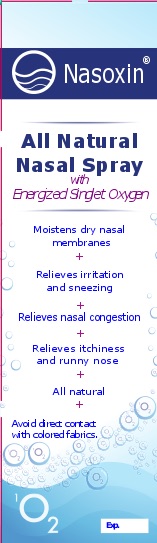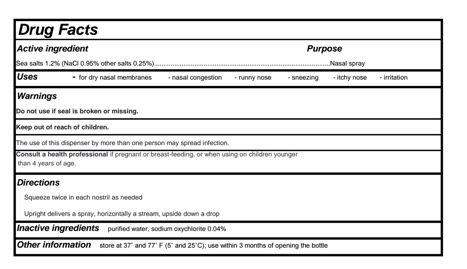 DRUG LABEL: NasoxinSpray
NDC: 70508-1601 | Form: SPRAY
Manufacturer: FRIANA LLC
Category: otc | Type: HUMAN OTC DRUG LABEL
Date: 20160419

ACTIVE INGREDIENTS: SODIUM CHLORIDE 1.2 mg/10 mL
INACTIVE INGREDIENTS: WATER; SODIUM HYPOCHLORITE

Nasoxin Nasal Spray

PACKAGE LABEL

ACTIVE INGREDIENT

Sodium Chloride (NaCl 0.95%, Sea salts 1.2%, other salts 0.25%)

Keep out of reach of children.

PURPOSE

Moisturizes nasal passages

INDICATIONS AND USAGE

for dry nasal membranes
nasal congestion
runny nose
sneezing
itchy nose
irritation

Do not use if seal is broken or missing.
The use of this dispenser by more than one person may spread infection.
If pregnant or breast-feeding, or when using on children younger than 4 years of age, consult a health professional.

DOSAGE AND ADMINISTRATION

Squeeze twice in each nostril as needed
Upright delivers a spray, horizontally a stream, upside down a drop

INACTIVE INGREDIENT

Purified water
Sodium Oxychlorite 0.04%